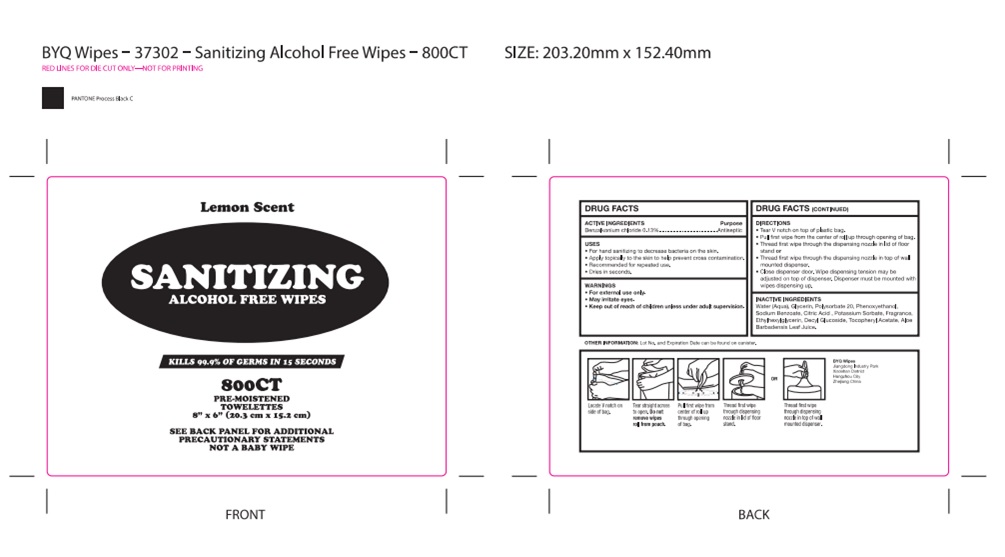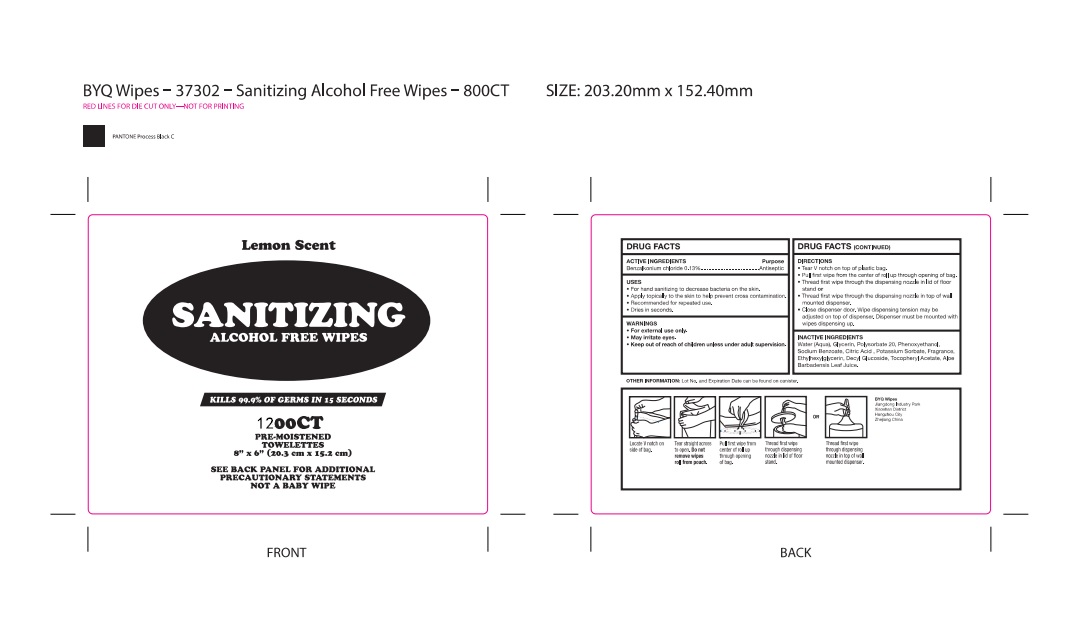 DRUG LABEL: sanitizing alcohol free wipe
NDC: 78882-101 | Form: CLOTH
Manufacturer: Hangzhou Boyiqing Hygiene Products Co., Ltd.
Category: otc | Type: HUMAN OTC DRUG LABEL
Date: 20230107

ACTIVE INGREDIENTS: BENZALKONIUM CHLORIDE 3.79 mg/1 1
INACTIVE INGREDIENTS: .ALPHA.-TOCOPHEROL ACETATE; PHENOXYETHANOL; SODIUM BENZOATE; ETHYLHEXYLGLYCERIN; GLYCERIN; WATER; POTASSIUM SORBATE; FRAGRANCE LAVENDER & CHIA F-153480; POLYSORBATE 20; CITRIC ACID MONOHYDRATE; DECYL GLUCOSIDE; ALOE VERA LEAF

sanitizing alcohol free wipe

sanitizing alcohol free wipe

Active Ingredient(s)

Benzalkonium Chloride 3.79mg/pcs. Purpose: Antiseptic

Purpose

Antiseptic, sanitizing alcohol free wipe

Use

sanitizing alcohol free wipe to help reduce bacteria that potentially can cause disease. For use when soap and water are not available.

Warnings

For external use only. Flammable. Keep away from heat or flame

Do not use

- in children less than 2 months of age
- on open skin wounds

When using this product keep out of eyes, ears, and mouth. In case of contact with eyes, rinse eyes thoroughly with water.
Stop use and ask a doctor if irritation or rash occurs. These may be signs of a serious condition.
Keep out of reach of children. If swallowed, get medical help or contact a Poison Control Center right away.

Stop use and ask a doctor if irritation or rash occurs. These may be signs of a serious condition.

Keep out of reach of children. If swallowed, get medical help or contact a Poison Control Center right away.

Directions

- Tear V notch on top of plastic bag.
- Pull first wipe from the center of roll up through opening of bag.
- Threod first wipe through the dispensing nozzle in lid of floor stand or.
- Threod first wipe through the dispensing nozzle in top of wall mounted dispenser.
- Close dispenser door, wipe dispensing tension may be adjusted on top of dispenser. Dispenser must be mounted with wipes dispensing up.
- Supervise children under 6 years of age when using this product to avoid swallowing.

Other information

- Store between 15-30C (59-86F)
- Avoid freezing and excessive heat above 40C (104F)

Inactive ingredients

water(Aqua)
Glycerin
polysorbate20
phenoxyethanol
sodium benzoate
citric acid
potassium sorbate
fragrance
Ethylhexylglycerin
decyl glucoside
tocopheryl acetate
ALOE barbodensis leaf juice